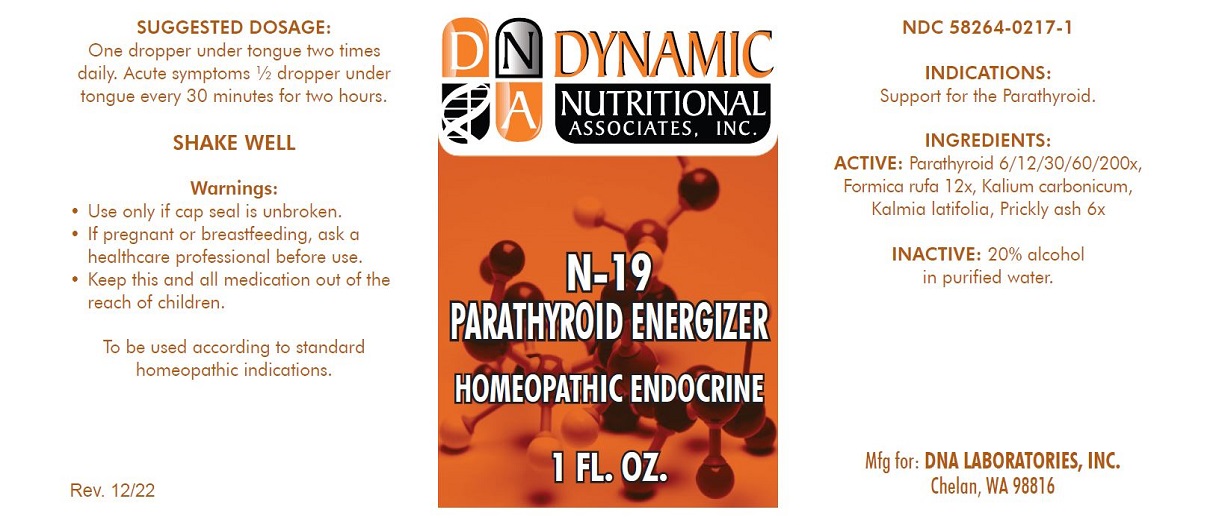 DRUG LABEL: N-19
NDC: 58264-0217 | Form: SOLUTION
Manufacturer: DNA Labs, Inc.
Category: homeopathic | Type: HUMAN OTC DRUG LABEL
Date: 20250109

ACTIVE INGREDIENTS: FORMICA RUFA 12 [hp_X]/1 mL; POTASSIUM CARBONATE 6 [hp_X]/1 mL; KALMIA LATIFOLIA WHOLE 6 [hp_X]/1 mL; ZANTHOXYLUM AMERICANUM BARK 6 [hp_X]/1 mL; BOS TAURUS PARATHYROID GLAND 200 [hp_X]/1 mL
INACTIVE INGREDIENTS: ALCOHOL; WATER

N-19

NDC 58264-0217-1

INDICATIONS

PURPOSE

Support for the Parathyroid.

INGREDIENTS

INACTIVE INGREDIENT

Formica rufa 12x, Kalium carbonicum 6x, Kalmia latifolia 6x, Xanthoxylum fraxineum 6x, Parathyroid 6/12/30/60/200x, 20% alcohol in purified water.

SUGGESTED DOSAGE

One dropper under tongue two times daily. Acute symptoms ½ dropper under tongue every 30 minutes for two hours.

STORAGE AND HANDLING

SHAKE WELL

Warnings

- Use only if cap seal is unbroken.

PREGNANCY OR BREAST FEEDING

- As with drugs if you are pregnant or nursing a baby seek professional advice before using this product.

KEEP OUT OF REACH OF CHILDREN

- Keep this and all medication out of the reach of children.

To be used according to standard homeopathic indications.

PRINCIPAL DISPLAY PANEL - 1 FL. OZ. Bottle Label

DYNAMIC
NUTRITIONAL
ASSOCIATES, INC.

N-19

PARATHYROID ENERGIZER

HOMEOPATHIC ENDOCRINE

1 FL. OZ.